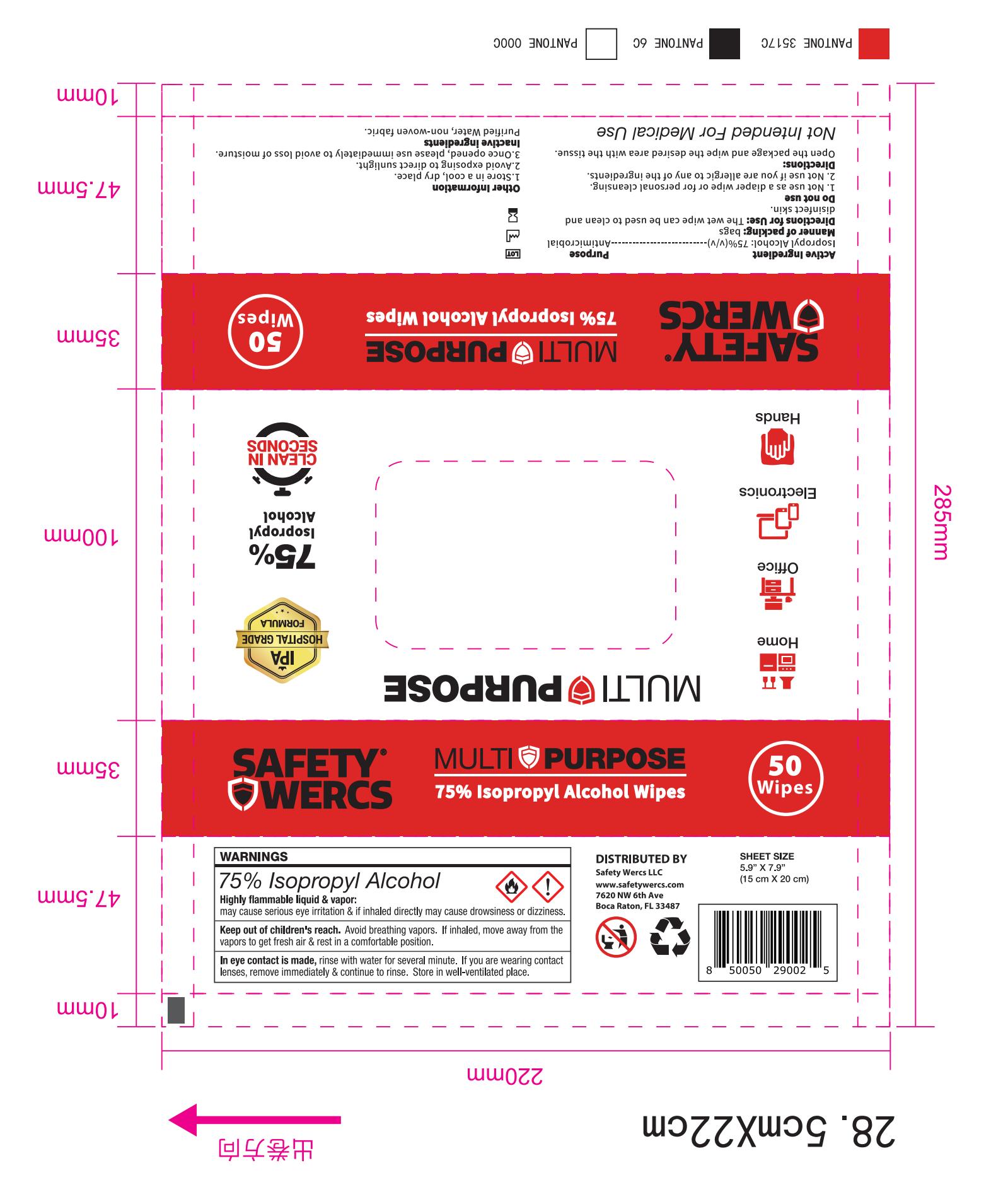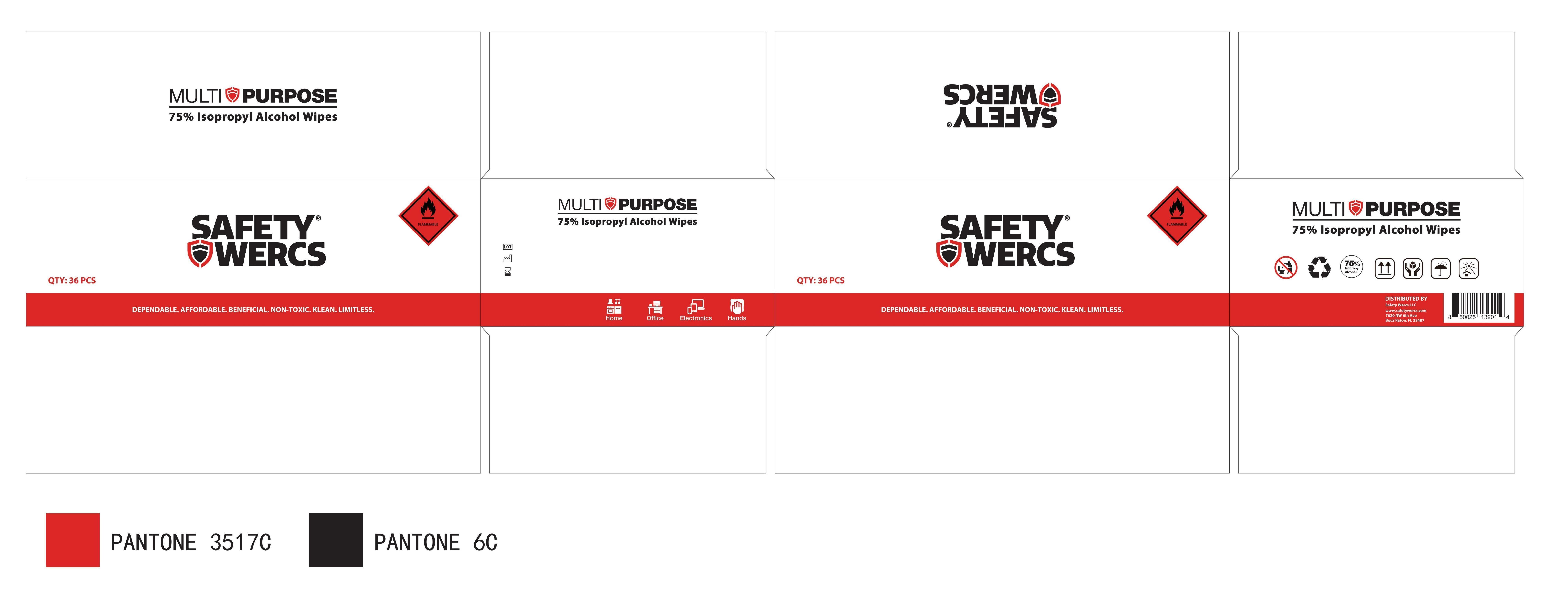 DRUG LABEL: 75% Isopropyl Alcohol Wipes
NDC: 84354-105 | Form: CLOTH
Manufacturer: safety wercs
Category: otc | Type: HUMAN OTC DRUG LABEL
Date: 20240626

ACTIVE INGREDIENTS: ISOPROPYL ALCOHOL 75 mL/100 mL
INACTIVE INGREDIENTS: WATER 25 mL/100 mL

75% Isopropyl Alcohol Wipes

Active Ingredient

Isopropyl Alcohol:75%(v/v)

Purpose

Antimicrobial

Uses

The wet wipe can be used to clean and disinfect skin.

Do not use

1.Not use as a diaper wipe or for personal cleansing.
2.Not use if you are allergic to any of the ingredients.

Directions

Open the package and wipe the desired area with the tissue.

Warnings

Highly flammable liquid&vapor:may cause serious eye irritation & if inhaled directly may cause drowsiness or dizziness.

Keep out of children's reach.Avoid breathing vapors. If inhaled, move away from the vapors to get fresh air & rest in a comfortable position.

In eye contact is made,rinse with water for several minute. If you are wearing contact lenses, remove immediately & continue to rinse. Store in well-ventilated place.

Keep out of reach of children section

Keep out of children's reach.Avoid breathing vapors. If inhaled, move away from the vapors to get fresh air & rest in a comfortable position.

other information

1.Store in a cool, dry place.

2.Avoid exposing to direct sunlight.

3.Once opened,please use immediately to avoid loss of moisture.

inactive ingredient

Purified Water

Non-woven fabric